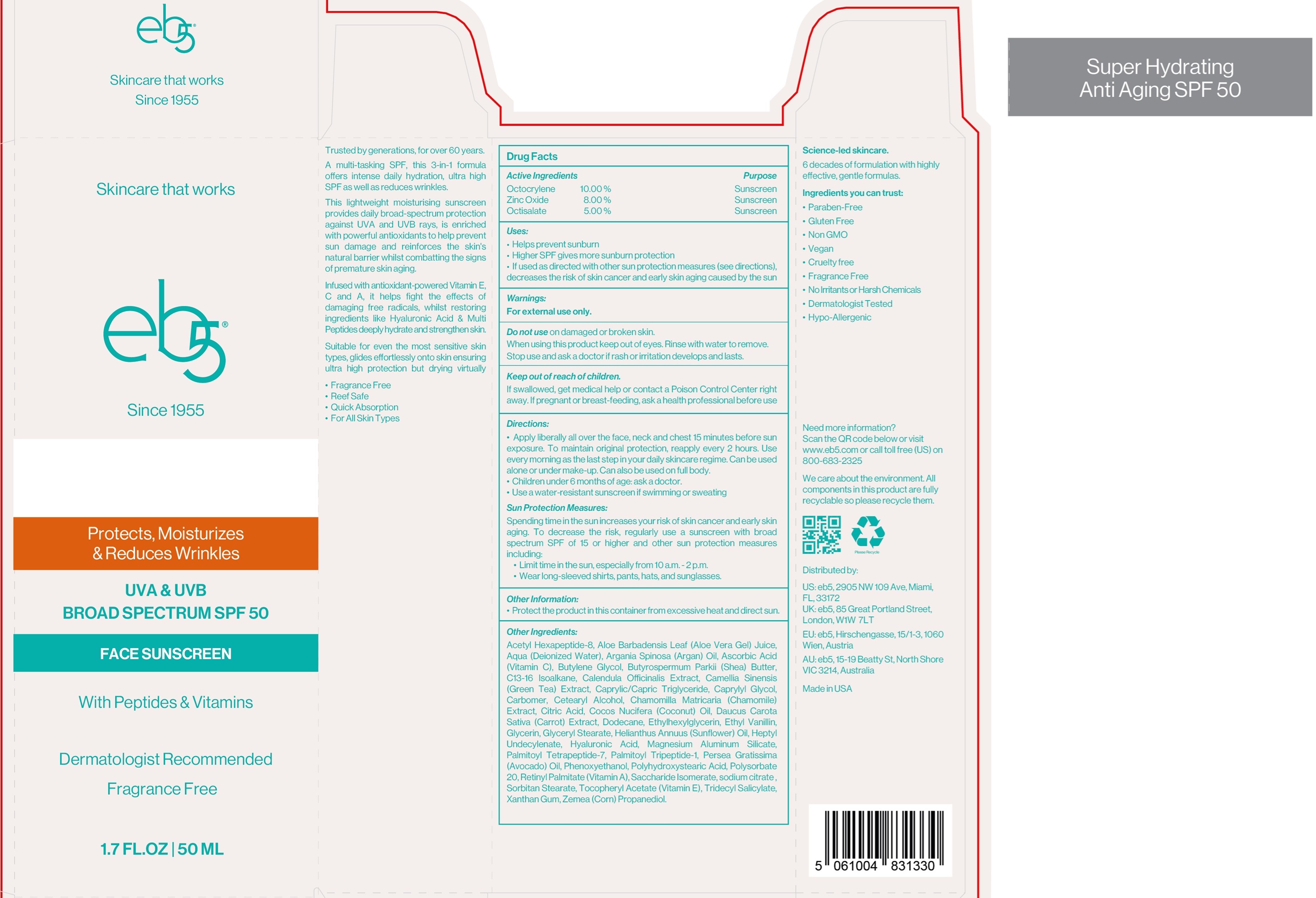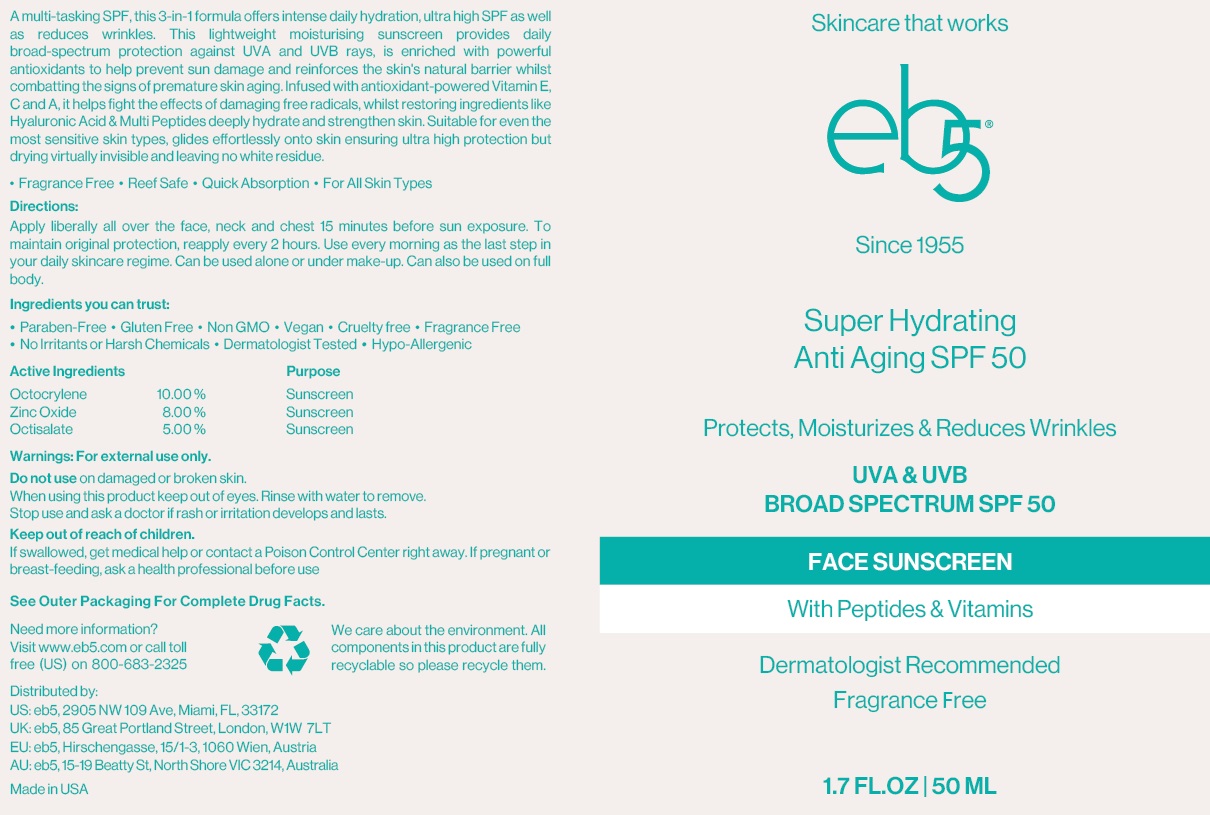 DRUG LABEL: EB-5 Super Hydrating Anti-Aging SPF-50
NDC: 84060-439 | Form: CREAM
Manufacturer: LIFE O, INC.
Category: otc | Type: HUMAN OTC DRUG LABEL
Date: 20240617

ACTIVE INGREDIENTS: OCTOCRYLENE 100 mg/1 mL; ZINC OXIDE 80 mg/1 mL; OCTISALATE 50 mg/1 mL
INACTIVE INGREDIENTS: ACETYL HEXAPEPTIDE-8 AMIDE; ALOE VERA LEAF; WATER; ASCORBIC ACID; BUTYLENE GLYCOL; C13-16 ISOPARAFFIN; CALENDULA OFFICINALIS FLOWER; GREEN TEA LEAF; MEDIUM-CHAIN TRIGLYCERIDES; CAPRYLYL GLYCOL; CARBOMER HOMOPOLYMER, UNSPECIFIED TYPE; CETOSTEARYL ALCOHOL; CHAMOMILE; CITRIC ACID MONOHYDRATE; COCONUT; CARROT; DODECANE; ETHYLHEXYLGLYCERIN; ETHYL VANILLIN; GLYCERIN; GLYCERYL MONOSTEARATE; HELIANTHUS ANNUUS FLOWERING TOP; HEPTYL UNDECYLENATE; HYALURONIC ACID; MAGNESIUM ALUMINUM SILICATE; PALMITOYL TETRAPEPTIDE-7; PALMITOYL TRIPEPTIDE-1; AVOCADO OIL; PHENOXYETHANOL; POLYSORBATE 20; VITAMIN A PALMITATE; SACCHARIDE ISOMERATE; SODIUM CITRATE, UNSPECIFIED FORM; SORBITAN MONOSTEARATE; .ALPHA.-TOCOPHEROL ACETATE; TRIDECYL SALICYLATE; XANTHAN GUM; CORN

EB-5 Super Hydrating Anti-Aging SPF-50

Active Ingredients

Octocrylene 10.00%

Zinc Oxide 8.00%

Octisalate 5.00%

Purpose

Sunscreen

Uses:

- Helps prevent sunburn
- Higher SPF gives more sunburn protection
- If used as directed with other sun protection measures (see directions), decreases the risk of skin cancer and early aging caused by the sun

Warnings

For external use only.

Do not use

on damaged or broken skin.

When using this product

keep out of eyes. Rinse with water to remove.

Stop use and ask a doctor

if rash or irritation develops and lasts.

Keep out of reach of children.

If swallowed, get medical help or contact a Poison Control Center right away. If pregnant or breast-feeding, ask a health professional before use

Directions:

- Apply liberally all over the face, neck and chest 15 minutes before sun exposure. To maintain original protection, reapply every 2 hours. Use every morning as the last step in your daily skincare regime. Can be used alone or under make-up. Can also be used on full body.
- Children under 6 months of age: ask a doctor.
- Use a water -resistant sunscreen if swimming or sweating

Sun Protection Measures

Sp ending time in the sun increases your risk of skin cancer and early skin aging. To decrease the risk, regularly use a sunscreen with broad spectrum SPF of 15 or higher and other sun protection measures including:

- Limit time in the sun, especially from 10 a.m.-2 p.m.
- Wear long-sleeved shirts, pants, hats, and sunglasses.

Other Information:

- Protect the product in this container from excessive heat and direct sun.

Other Ingredients:

Acetyl Hexapeptide-8, Aloe Barbadensis Leaf (Aloe Vera Gel) Juice, Aqua (Deionized Water), Argania Spinosa (Argan) Oil, Ascorbic Acid (Vitamin C), Butylene Glycol, Butyrispermum Parkii (Shea) Butter, C13-16 Isoalkane, Calendula Officinalis Extract, Camellia Sinensis (Green Tea) Extract, Caprylic/Capric Triglycerin, Caprylyl Glycol, Carbomer, Cetearyl Alcohol, Chamomilla Matricaria (Chamomile) Extract, Citric Acid, Coco Nucifera (Coconut) Oil, Daucus Carota Sativa (Carrot) Extract, Dodecane, Ethylhexlyglycerin, Ethyl Vanillin, Glycerin, Glyceryl Stearate, Helianthus Annuus (Sunfloer) Oil, Heptyl Undecylenate, Hyaluronic Acid, Magnesium Aluminum Silicate, Palmitoyl Tetrapeptide-7, Palmitoyl Tripeptide-1, Persea Gratissima (Avocado) Oil, Phenoxyethanol, Polyhydroxystearic Acid, Polysorbate 20, Retinyl Palmitate (Vitamin A), Saccharide Isomerate, Sodium citrate, Sorbitan Stearate, Tocopheryl Acetate (Vitamin E), Tridecyl Salicylate, Xanthan Gum, Zemea (Corn) Propanediol.